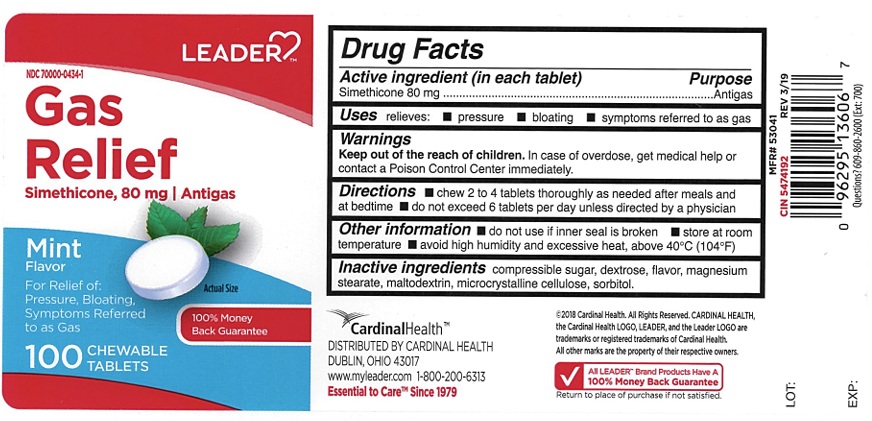 DRUG LABEL: Leader Gas relief
NDC: 70000-0434 | Form: TABLET, CHEWABLE
Manufacturer: CARDINAL HEALTH 110, LLC. DBA LEADER
Category: otc | Type: Human OTC Drug Label
Date: 20241217

ACTIVE INGREDIENTS: DIMETHICONE 80 mg/1 1
INACTIVE INGREDIENTS: SUGARCANE; MALTODEXTRIN; DEXTROSE, UNSPECIFIED FORM; MAGNESIUM STEARATE; MICROCRYSTALLINE CELLULOSE; SORBITOL

Leader Gas Relief Chewable Tablets

ACTIVE INGREDIENT(in each tablet)

Simethicone 80 mg

PURPOSE

Antigas

USE(S)

relieves:

- pressure
- bloating
- symptoms referred to as gas

WARNINGS

.

KEEP OUT OF REACH OF CHILDREN

In case of overdose, get medical help or contact a Poison Control Center immediately.

DIRECTIONS

- chew 2 to 4 tablets thoroughly as needed after meals and at bedtime
- do not exceed 6 tablets per day unless directed by a physician

OTHER INFORMATION

- do not use if inner seal is broken
- store at room temperature
- avoid high humidity and excessive heat, above 40oC (104oF)

INACTIVE INGREDIENTS

compressible sugar, dextrose, flavor, magnesium stearate, maltodextrin, microcrystalline cellulose, sorbitol.

PRINCIPAL DISPLAY PANEL

DC 70000-0434-1
LEADER™
Gas Relief
Simethicone, 80 mg
Antigas
Mint Flavor
For Relief of :
Pressure, Bloating, Symptoms Referred to as Gas
100 CHEWABLE TABLETS